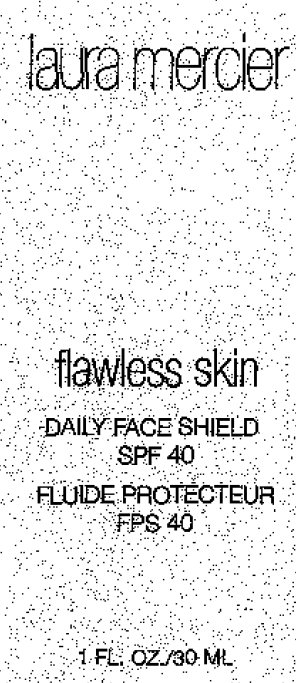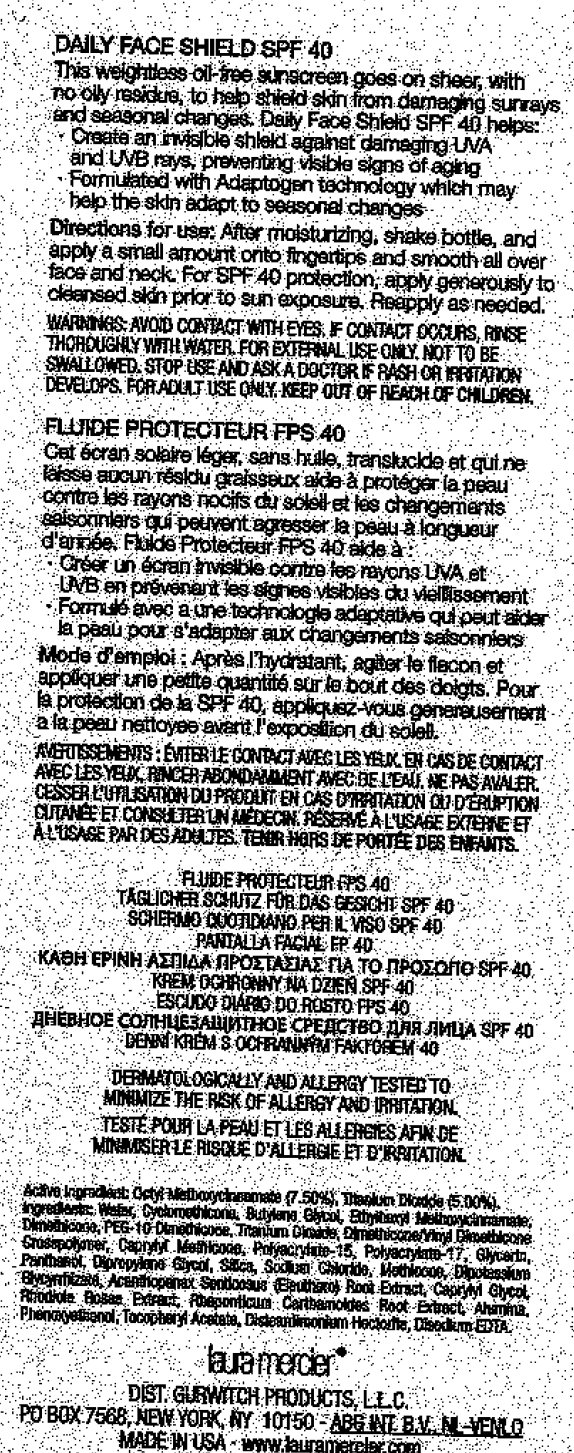 DRUG LABEL: Laura Mercier Flawless Skin Daily Face Shield SPF 40
NDC: 65342-2340 | Form: LIQUID
Manufacturer: Gurwitch Products, LLC
Category: otc | Type: HUMAN OTC DRUG LABEL
Date: 20231212

ACTIVE INGREDIENTS: OCTINOXATE 75 mg/1 mL; TITANIUM DIOXIDE 50 mg/1 mL
INACTIVE INGREDIENTS: WATER; CYCLOMETHICONE; BUTYLENE GLYCOL; DIMETHICONE; GLYCERIN; PANTHENOL; SILICON DIOXIDE; SODIUM CHLORIDE; GLYCYRRHIZINATE DIPOTASSIUM; ELEUTHERO; CAPRYLYL GLYCOL; ALUMINUM OXIDE; PHENOXYETHANOL; EDETATE DISODIUM

Laura Mercier Flawless Skin Daily Face Shield SPF 40

Active Ingredient: Octyl Methoxycinnamate (7.50%), Titanium Dioxide (5.00%).

PURPOSE

FOR ADULT USE ONLY.

WARNINGS

WARNINGS: FOR EXTERNAL USE ONLY. NOT TO BE SWALLOWED

WHEN USING

AVOID CONTACT WITH EYES. IF CONTACT OCCURS, RINSE THOROUGHLY WITH WATER

STOP USE AND ASK A DOCTOR IF RASH OR IRRITATION DEVELOPS.

KEEP OUT OF REACH OF CHILDREN.

DOSAGE AND ADMINISTRATION

Directions for use: After moisturizing, shake bottle, and apply a small amount onto fingertips and smooth all over face and neck. For SPF 40 protection, apply generously to cleansed skin prior to sum exposure. Reapply as needed.

DESCRIPTION

DAILY FACE SHIELD SPF 40 This weightless oil-free sunscreen goes on sheer, with no oily residue, to help shield skin from damaging sunrays and seasonal changes. Daily Face Shield SPF 40 helps: - Create an invisible shield against damaging UVA and UVB rays, preventing visible signs of aging - Formulated with Adaptogen technology which may help the skin adapt to seasonal changes. DERMATOLOGICALLY AND ALLERGY TESTED TO MINIMIZE THE RISK OF ALLERGY AND IRRITATION. DIST. GURWITCH PRODUCTS, L.L.C, PO BOX 7568, NEW YORK, NY 10150 - ABG INT B.V. NL-VENLO MADE IN USA - www.lauramereler.com

PACKAGE LABEL

laura mercier flawless skin DAILY FACE SHIELD SPF 40 1 FL. OZ/30 ML

PACKAGE LABEL

DAILY FACE SHIELD SPF 40 This weightless oil-free sunscreen goes on sheer, with no oily residue, to help shield skin from damaging sunrays and seasonal changes. Daily Face Shield SPF 40 helps: - Create an invisible shield against damaging UVA and UVB rays, preventing visible signs of aging - Formulated with Adaptogen technology which may help the skin adapt to seasonal changes. DERMATOLOGICALLY AND ALLERGY TESTED TO MINIMIZE THE RISK OF ALLERGY AND IRRITATION. DIST. GURWITCH PRODUCTS, L.L.C, PO BOX 7568, NEW YORK, NY 10150 - ABG INT B.V. NL-VENLO MADE IN USA - www.lauramereler.com